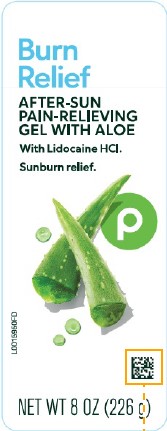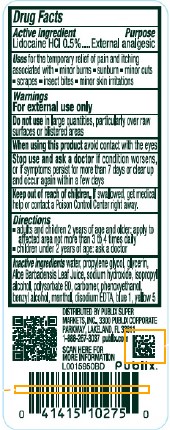 DRUG LABEL: burnrelief
NDC: 56062-942 | Form: GEL
Manufacturer: Publix Super Markets, Inc.
Category: otc | Type: HUMAN OTC DRUG LABEL
Date: 20260205

ACTIVE INGREDIENTS: LIDOCAINE HYDROCHLORIDE 5 mg/1 g
INACTIVE INGREDIENTS: WATER; PROPYLENE GLYCOL; GLYCERIN; ALOE VERA LEAF; SODIUM HYDROXIDE; ISOPROPYL ALCOHOL; POLYSORBATE 80; CARBOMER HOMOPOLYMER, UNSPECIFIED TYPE; PHENOXYETHANOL; BENZYL ALCOHOL; MENTHOL; EDETATE DISODIUM; FD&C BLUE NO. 1; FD&C YELLOW NO. 5

Publix 005.003/005AE
Sunburn Relief Gel

Active ingredient

Lidocaine HCl 0.5 %

purpose

External analgesic

Uses

for the temporary relief of pain and itching associated with

- minor burns
- sunburn
- minor cuts
- scrapes
- insect bites
- minor skin irritations

warnings

For external use only

Do not use

in large quantities, particularly over raw surfaces or blistered areas

When using this product

avoid contact with the eyes

Stop use and ask a doctor if

condition worsens, or if symptoms persist for more than 7 days or clear up and occur again within a few days

Keep out of reach of children.

If swallowed, get medical help or contact a Poison Control Center right away.

Directions

- adults and children 2 years of age and older: apply to affected area not more than 3 to 4 times daily
- children under 2 years of age: ask a doctor

inactive ingredients

water, propylene glycol, glycerin, Aloe Barbadensis Leaf Juice, sodium hydroxide, isopropyl alcohol, polysorbate 80, carbomer, phenoxyethanol, benzyl alcohol, menthol, disodium EDTA, blue 1, yellow 5

ADVERSE REACTION

DISTRIBUTED BY PUBLIX SUPER MARKETS, INC.,

3300 PUBLIX CORPORATE PARKWAY

LAKELAND, FL 33811

1-888-267-3037 publix.com

SCAN HERE FOR MORE INFORMATION

PUBLIX

principal display panel

Burn Relief

AFTER-SUN

PAIN-RELIEVING

GEL WITH ALOE

WITH LIDOCAINE HCl.

SUNBURN RELIEF.

P

NET WT 8 OZ (226 g)